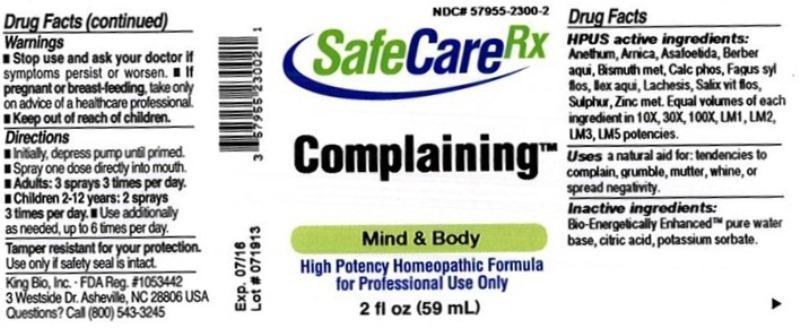 DRUG LABEL: Complaining
NDC: 57955-2300 | Form: LIQUID
Manufacturer: King Bio Inc.
Category: homeopathic | Type: HUMAN OTC DRUG LABEL
Date: 20130827

ACTIVE INGREDIENTS: DILL 10 [hp_X]/59 mL; ARNICA MONTANA 10 [hp_X]/59 mL; ASAFETIDA 10 [hp_X]/59 mL; MAHONIA AQUIFOLIUM ROOT BARK 10 [hp_X]/59 mL; BISMUTH 10 [hp_X]/59 mL; TRIBASIC CALCIUM PHOSPHATE 10 [hp_X]/59 mL; FAGUS SYLVATICA FLOWERING TOP 10 [hp_X]/59 mL; ILEX AQUIFOLIUM FLOWERING TOP 10 [hp_X]/59 mL; LACHESIS MUTA VENOM 10 [hp_X]/59 mL; SALIX ALBA FLOWERING TOP 10 [hp_X]/59 mL; SULFUR 10 [hp_X]/59 mL; ZINC 10 [hp_X]/59 mL
INACTIVE INGREDIENTS: WATER; CITRIC ACID MONOHYDRATE; POTASSIUM SORBATE

Complaining™

Drug Facts

____________________________________________________________________________________________________________

HPUS active ingredients: Anethum graveolens, Arnica montana, Asafoetida, Berberis aquifolium, Bismuthum metallicum, Calcarea phosphorica, Fagus sylvatica, flos, Ilex aquifolium, Lachesis mutus, Salix vitellina, flos, Sulphur, Zincum metallicum. Equal volumes of each ingredient in 10X, 30X, 100X, LM1, LM2, LM3, LM5 potencies.

INDICATIONS AND USAGE

Uses a natural aid for:

- tendencies to complain
- grumble
- mutter, whine or spread negativity

INACTIVE INGREDIENT

Inactive ingredients: Bio-Energetically Enhanced pure water base, citric acid, potassium sorbate.

Warnings

- Stop use and ask your doctor if symptoms persist or worsen.
- If pregnant or breast-feeding, take only on advice of a healthcare professional.

- Keep out of reach of children.

Directions:

- Initially, depress pump until primed.
- Spray one dose directly into mouth.
- Adults: 3 sprays 3 times per day.
- Children 2-12 years: 2 sprays 3 times per day.
- Use additionally as needed, up to 6 times per day.

OTHER SAFETY INFORMATION

Tamper resistant for your protection. Use only if safety seal is intact.

PURPOSE

Uses a natural aid for: tendencies to complain, grumble, mutter, whine or spread negativity.